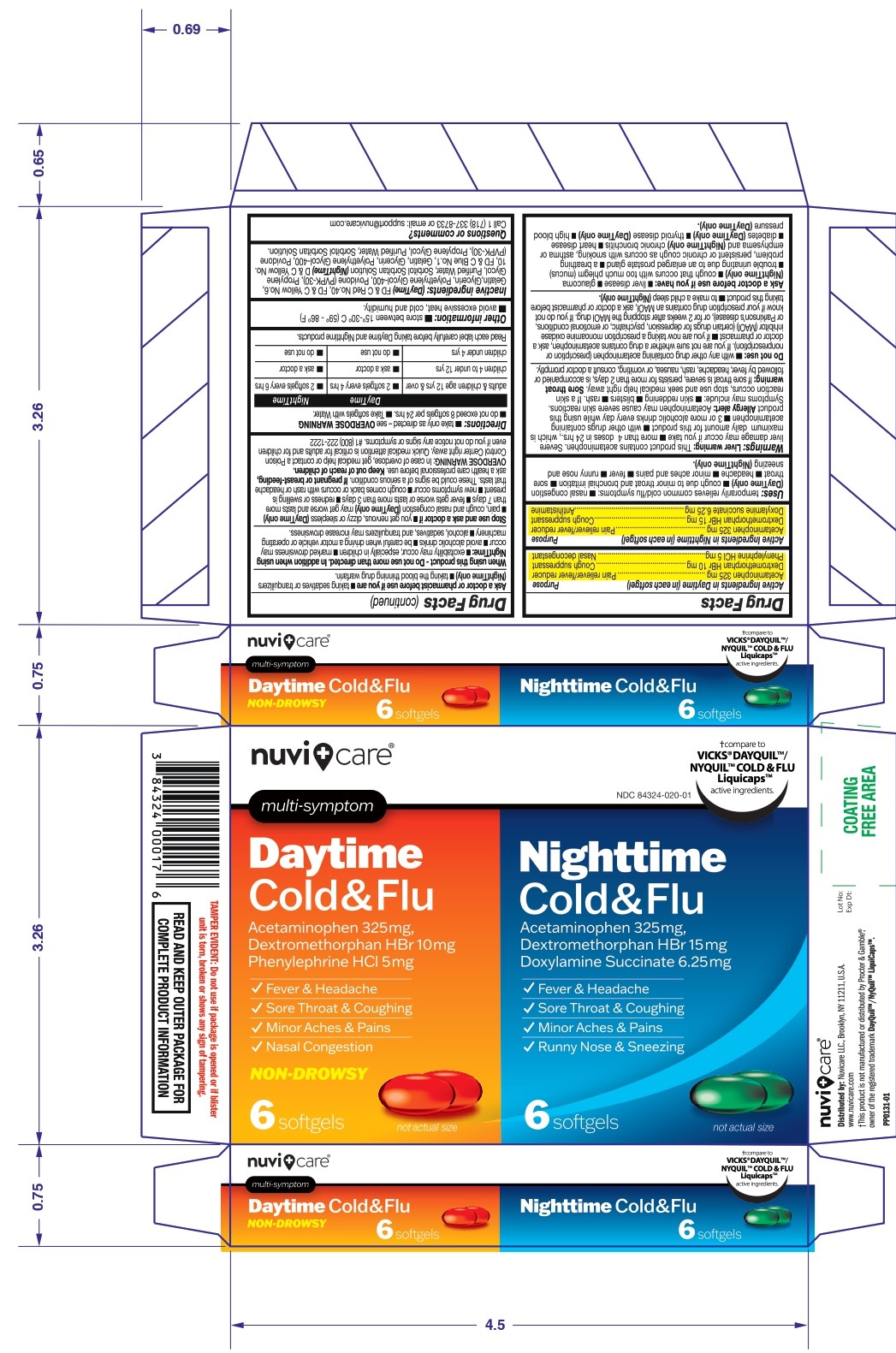 DRUG LABEL: Nuvicare DayTime and NightTime Cold and Flu
NDC: 84324-020 | Form: KIT | Route: ORAL
Manufacturer: NUVICARE LLC
Category: otc | Type: HUMAN OTC DRUG LABEL
Date: 20250609

ACTIVE INGREDIENTS: ACETAMINOPHEN 325 mg/1 1; DEXTROMETHORPHAN HYDROBROMIDE 10 mg/1 1; PHENYLEPHRINE HYDROCHLORIDE 5 mg/1 1; ACETAMINOPHEN 325 mg/1 1; DEXTROMETHORPHAN HYDROBROMIDE 15 mg/1 1; DOXYLAMINE SUCCINATE 6.25 mg/1 1
INACTIVE INGREDIENTS: POLYETHYLENE GLYCOL 400; PROPYLENE GLYCOL; POVIDONE; Gelatin; Sorbitol; GLYCERIN; FD&C RED NO. 40; FD&C YELLOW NO. 6; POLYETHYLENE GLYCOL 400; PROPYLENE GLYCOL; POVIDONE; Gelatin; Sorbitol; GLYCERIN; FD&C BLUE NO. 1; D&C YELLOW NO. 10

Nuvicare DayTime and NightTime Cold and Flu Softgel Combo Pack

Active ingredients

Active ingredients in DayTime (in each softgel)

Acetaminophen 325mg

Dextromethorphan HBr 10mg

Phenylephrine HCl 5mg

Active ingredients in NightTime (in each softgel)

Acetaminophen 325mg

Dextromethorphan HBr 15mg

Doxylamine Succinate 6.25 mg

Purpose

DayTime

Acetaminophen 325mg.....................Pain reliever/fever reducer
Dextromethorphan HBr 10mg..................... Cough suppressant
Phenylephrine HCl 5mg ............................. Nasal decongestant

NightTime

Acetaminophen 325mg.....................Pain reliever/fever reducer
Dextromethorphan HBr 15mg..................... Cough suppressant
Doxylamine succinate 6.25 mg ............................. Antihistamine

Uses:

temporarily relieves common cold/flu symptoms:

■ nasal congestion (DayTime Only)

■ cough due to minor throat & bronchial irritation

■ sore throat

■ headache

■ minor aches & pains

■ fever

■ Runny nose and sneezing (NightTime only)

Warning

Liver warning: This product contains acetaminophen. Severe liver damage may occur if you take:

■ more than 4 doses in 24 hrs, which is the maximum daily amount for this product ■ with other drugs containing acetaminophen ■ 3 or more alcoholic drinks every day while using this product.

Allergy Alert: acetamenophen may cause severe skin recations. Symptoms may include:

■ skin reddening ■ blisters ■ rash. if a skin reactions occurs, stop use and seek medical help right away.

Sore throat warning: If sore throat is severe, persists for more than 2 days, is accompanied or followed by fever, headache, rash, nausea, or vomiting,consult a doctor promptly.

Do not use:

- with any other drug containing acetaminophen (prescription or nonprescription). If you are not sure whether a drug contains acetaminophen, ask a doctor or pharmacist
- if you are now taking a prescription monoamine oxidase inhibitor (MAOI) (certain drugs for depression, psychiatric or emotional conditions, or Parkinson's disease), or for 2 weeks after stopping the MAOI drug. If you do not know if your prescription drug contains an MAOI, ask a doctor or pharmacist before taking this product.
- to make a child sleep (NightTime Only).

Ask a doctor before use if you have

■ liver disease

■ Glaucoma (NightTime Only)

■ cough that occurs with too much phlegm (mucus)

■ trouble urinating due to enlarged prostate gland

■ a breathing problem, persistent or chronic cough as occurs with smoking, asthma, or emphysema and (NightTime Only) chronic Bronchitis

■ heart disease

■ diabetes (DayTime Only)

■ thyroid disease (DayTime Only)

■ high blood pressure (DayTime Only)

Ask a doctor or pharmacist before use if you are

- taking sedatives or tranquilizers (NightTime Only)
- taking the blood thinning drug warfarin

When using this product-do not use more than directed. In addition when using NightTime:

- excitability may occur, especially in children
- marked drowsiness may occur
- avoid alcoholic drinks
- be careful when driving a motor vehicle or operating machiner
- alcohol, sedative and tranquilizers may increase drowsiness

Stop use and ask a doctor if

- you get nervous, dizzy or sleepless (DayTime Only)

- pain, cough or nasal congestion (DayTime only) may get worse or last more than 7 days
- fever gets worse or lasts more than 3 days
- redness or swelling is present
- new symptoms occur
- cough comes back, or occurs with rash or headache that lasts. These could be signs of a serious condition.

PREGNANCY OR BREAST FEEDING

If pregnant or breast-feeding, ask a health care professional before use.

Keep out of reach of children.

OVERDOSAGE

OVERDOSE WARNING: In case of overdose, get medical help or contact a Poison Control Center right away. Quick medical attention is critical for adults and for children even if you do not notice any signs or symptoms. # 1 (800) 222-1222

Directions

■ take only as directed- see OVERDOSE WARNING

■ do not exceed 8 softgels per 24 hrs.

■ Take softgels with water

 | DayTime | NightTime
Adults and children age 12 yrs and over | 2 softgels every 4 hrs. | 2 softgels every 6 hrs.
Children 4 to under 12 yrs | ask a doctor | ask a doctor
Children under 4 yrs | do not use | do not use

Read each label carefully before taking Daytime and Nighttime products.

Other information

■ store between 15-30°C (59-86 °F)

■ avoid excessive heat, cold and humidity

Inactive ingredients

(Daytime) FD&C Red No. 40, FD&C Yellow No. 6, Gelatin, Glycerin, Polyethylene glycol-400, Povidone (PVPK-30), Propylene glycol,
Purified water, Sorbitol sorbitan solution

(Nighttime) D&C Yellow No. 10, FD&C Blue No. 1, Gelatin, Glycerin, Polyethylene glycol-400, Povidone (PVPK-30), Propylene glycol, Purified water, Sorbitol sorbitan solution

Questions or Comments?

Call 1 (718) 337-8733 or email: support@nuvicare.com